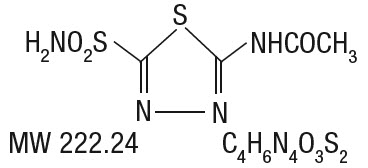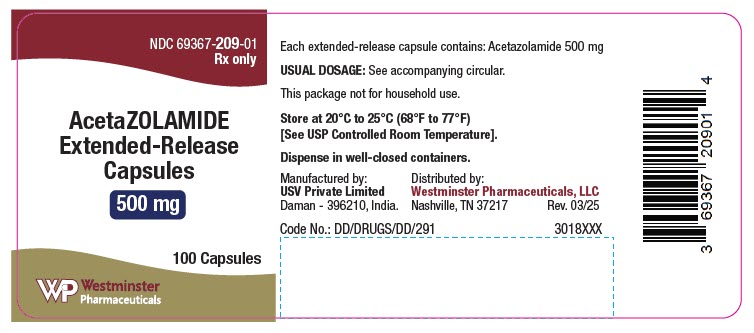 DRUG LABEL: Acetazolamide
NDC: 69367-209 | Form: CAPSULE, EXTENDED RELEASE
Manufacturer: Westminster Pharmaceuticals, LLC
Category: prescription | Type: HUMAN PRESCRIPTION DRUG LABEL
Date: 20260217

ACTIVE INGREDIENTS: ACETAZOLAMIDE 500 mg/1 1
INACTIVE INGREDIENTS: MICROCRYSTALLINE CELLULOSE; SODIUM LAURYL SULFATE; HYDROXYPROPYL CELLULOSE, UNSPECIFIED; TALC; FD&C GREEN NO. 3; FERROSOFERRIC OXIDE; FERRIC OXIDE YELLOW; TITANIUM DIOXIDE; GELATIN, UNSPECIFIED; SHELLAC; PROPYLENE GLYCOL; POTASSIUM HYDROXIDE

Acetazolamide Extended-Release Capsules

Rev. 3/2025

DESCRIPTION

Acetazolamide Extended-Release Capsules are an inhibitor of the enzyme carbonic anhydrase.

Acetazolamide is a white to faintly yellowish white crystalline, odorless powder, weakly acidic, very slightly soluble in water, and slightly soluble in alcohol. The chemical name for acetazolamide is N-(5-Sulfamoyl-1,3,4-thiadiazol-2-yl) acetamide and has the following chemical structure:

Acetazolamide Extended-Release Capsules are extended-release capsules, for oral administration, each containing 500 mg of acetazolamide and the following inactive ingredients: Microcrystalline cellulose, sodium lauryl sulfate, hydroxypropyl cellulose and talc.

The ingredients in the capsule shell are FD&C green # 3, FDA/E172 black iron oxide, FDA/E172 yellow iron oxide, titanium dioxide and gelatin.

The ingredients in the imprinting ink are shellac, propylene glycol, potassium hydroxide and black iron oxide.

CLINICAL PHARMACOLOGY

Acetazolamide is a potent carbonic anhydrase inhibitor, effective in the control of fluid secretion (e.g., some types of glaucoma), in the treatment of certain convulsive disorders (e.g., epilepsy), and in the promotion of diuresis in instances of abnormal fluid retention (e.g., cardiac edema).

Acetazolamide is not a mercurial diuretic. Rather, it is a non-bacteriostatic sulfonamide possessing a chemical structure and pharmacological activity distinctly different from the bacteriostatic sulfonamides.

Acetazolamide is an enzyme inhibitor that acts specifically on carbonic anhydrase, the enzyme that catalyzes the reversible reaction involving the hydration of carbon dioxide and the dehydration of carbonic acid. In the eye, this inhibitory action of acetazolamide decreases the secretion of aqueous humor and results in a drop in intraocular pressure, a reaction considered desirable in cases of glaucoma and even in certain non-glaucomatous conditions. Evidence seems to indicate that acetazolamide has utility as an adjuvant in treatment of certain dysfunctions of the central nervous system (e.g., epilepsy). Inhibition of carbonic anhydrase in this area appears to retard abnormal, paroxysmal, excessive discharge from central nervous system neurons. The diuretic effect of acetazolamide is due to its action in the kidney on the reversible reaction involving hydration of carbon dioxide and dehydration of carbonic acid. The result is renal loss of HCO3 ion, which carries out sodium, water, and potassium. Alkalinization of the urine and promotion of diuresis are thus affected. Alteration in ammonia metabolism occurs due to increased reabsorption of ammonia by the renal tubules as a result of urinary alkalinization.

Acetazolamide Extended-Release Capsules provide prolonged action to inhibit aqueous humor secretion for 18 to 24 hours after each dose, whereas tablets act for only eight to 12 hours. The prolonged continuous effect of pellets permits a reduction in dosage frequency.

Plasma concentrations of acetazolamide peak from three to six hours after administration of Acetazolamide Extended-Release Capsules, compared to one to four hours with tablets. Food does not affect bioavailability of Acetazolamide Extended-Release Capsules.

Placebo-controlled clinical trials have shown that prophylactic administration of acetazolamide at a dose of 250 mg every eight to 12 hours (or a 500 mg controlled release capsule once daily) before and during rapid ascent to altitude results in fewer and/or less severe symptoms of acute mountain sickness (AMS) such as headache, nausea, shortness of breath, dizziness, drowsiness, and fatigue. Pulmonary function (e.g., minute ventilation, expired vital capacity, and peak flow) is greater in the acetazolamide treated group, both in subjects with AMS and asymptomatic subjects. The acetazolamide treated climbers also had less difficulty in sleeping.

INDICATIONS AND USAGE

For adjunctive treatment of: chronic simple (open-angle) glaucoma, secondary glaucoma, and preoperatively in acute angle-closure glaucoma where delay of surgery is desired in order to lower intraocular pressure. Acetazolamide is also indicated for the prevention or amelioration of symptoms associated with acute mountain sickness despite gradual ascent.

CONTRAINDICATIONS

Hypersensitivity to acetazolamide or any excipients in the formulation. Since acetazolamide is a sulfonamide derivative, cross sensitivity between acetazolamide, sulfonamides and other sulfonamide derivatives is possible.

Acetazolamide therapy is contraindicated in situations in which sodium and/or potassium blood serum levels are depressed, in cases of marked kidney and liver disease or dysfunction, in suprarenal gland failure, and in hyperchloremic acidosis. It is contraindicated in patients with cirrhosis because of the risk of development of hepatic encephalopathy.

Long-term administration of acetazolamide is contraindicated in patients with chronic non-congestive angle-closure glaucoma since it may permit organic closure of the angle to occur while the worsening glaucoma is masked by lowered intraocular pressure.

WARNINGS

Fatalities have occurred, although rarely, due to severe reactions to sulfonamides including Stevens-Johnson syndrome, toxic epidermal necrolysis, fulminant hepatic necrosis, anaphylaxis, agranulocytosis, aplastic anemia, and other blood dyscrasias. Sensitizations may recur when a sulfonamide is readministered irrespective of the route of administration. If signs of hypersensitivity or other serious reactions occur, discontinue use of this drug.

Caution is advised for patients receiving concomitant high-dose aspirin and acetazolamide, as anorexia, tachypnea, lethargy, metabolic acidosis, coma, and death have been reported.

PRECAUTIONS

General

Increasing the dose does not increase the diuresis and may increase the incidence of drowsiness and/or paresthesia. Increasing the dose often results in a decrease in diuresis. Under certain circumstances, however, very large doses have been given in conjunction with other diuretics in order to secure diuresis in complete refractory failure.

Choroidal effusion and choroidal detachment have been reported after the use of acetazolamide in the post-operative period following ophthalmic surgery. Discontinue acetazolamide if choroidal effusion and/or choroidal detachment is suspected.

Information for Patients

Adverse reactions common to all sulfonamide derivatives may occur: anaphylaxis, fever, rash (including erythema multiforme, Stevens-Johnson syndrome, toxic epidermal necrolysis), crystalluria, renal calculus, bone marrow depression, thrombocytopenic purpura, hemolytic anemia, leukopenia, pancytopenia, and agranulocytosis. Caution is advised for early detection of such reactions and the drug should be discontinued and appropriate therapy instituted.

In patients with pulmonary obstruction or emphysema where alveolar ventilation may be impaired, Acetazolamide which may precipitate or aggravate acidosis should be used with caution.

Gradual ascent is desirable to try to avoid acute mountain sickness. If rapid ascent is undertaken and acetazolamide is used, it should be noted that such use does not obviate the need for prompt descent if severe forms of high altitude sickness occur, i.e., high altitude pulmonary edema (HAPE) or high altitude cerebral edema.

Caution is advised for patients receiving concomitant high-dose aspirin and acetazolamide, as anorexia, tachypnea, lethargy, metabolic acidosis, coma, and death have been reported (see WARNINGS).

Both increases and decreases in blood glucose have been described in patients treated with acetazolamide. This should be taken into consideration in patients with impaired glucose tolerance or diabetes mellitus.

Acetazolamide treatment may cause electrolyte imbalances, including hyponatremia and hypokalemia, as well as metabolic acidosis. Therefore, periodic monitoring of serum electrolytes is recommended. Particular caution is recommended in patients with conditions that are associated with, or predispose a patient to, electrolyte and acid/base imbalances, such as patients with impaired renal function (including elderly patients; see PRECAUTIONS, Geriatric Use), patients with diabetes mellitus, and patients with impaired alveolar ventilation.

Some adverse reactions to acetazolamide, such as drowsiness, fatigue, and myopia, may impair the ability to drive and operate machinery.

Laboratory Tests

To monitor for hematologic reactions common to all sulfonamides, it is recommended that a baseline CBC and platelet count be obtained on patients prior to initiating acetazolamide therapy and at regular intervals during therapy. If significant changes occur, early discontinuance and institution of appropriate therapy are important. Periodic monitoring of serum electrolytes is recommended.

Drug Interactions

Aspirin - See WARNINGS

Acetazolamide modifies phenytoin metabolism with increased serum levels of phenytoin. This may increase or enhance the occurrence of osteomalacia in some patients receiving chronic phenytoin therapy. Caution is advised in patients receiving chronic concomitant therapy. By decreasing the gastrointestinal absorption of primidone, Acetazolamide may decrease serum concentrations of primidone and its metabolites, with a consequent possible decrease in anticonvulsant effect. Caution is advised when beginning, discontinuing, or changing the dose of acetazolamide in patients receiving primidone.

Because of possible additive effects with other carbonic anhydrase inhibitors, concomitant use is not advisable.

Acetazolamide may increase the effects of other folic acid antagonists.

Acetazolamide decreases urinary excretion of amphetamine and may enhance the magnitude and duration of their effect.

Acetazolamide reduces urinary excretion of quinidine and may enhance its effect.

Acetazolamide may prevent the urinary antiseptic effect of methenamine.

Acetazolamide increases lithium excretion and the lithium may be decreased. Acetazolamide and sodium bicarbonate used concurrently increase the risk of renal calculus formation. Acetazolamide may elevate cyclosporine levels.

Drug/laboratory test interactions

Sulfonamides may give false negative or decreased values for urinary phenolsulfonphthalein and phenol red elimination values for urinary protein, serum non-protein, and serum uric acid. Acetazolamide may produce an increased level of crystals in the urine.

Acetazolamide interferes with the HPLC method of assay for theophylline. Interference with the theophylline assay by acetazolamide depends on the solvent used in the extraction; acetazolamide may not interfere with other assay methods for theophylline.

Carcinogenesis, Mutagenesis, Impairment of Fertility

Long-term studies in animals to evaluate the carcinogenic potential of acetazolamide have not been conducted. In a bacterial mutagenicity assay, Acetazolamide was not mutagenic when evaluated with and without metabolic activation.

The drug had no effect on fertility when administered in the diet to male and female rats at a daily intake of up to 4 times the recommended human dose of 1000 mg in a 50 kg individual.

Pregnancy

Teratogenic effects

Acetazolamide, administered orally or parenterally, has been shown to be teratogenic (defects of the limbs) in mice, rats, hamsters, and rabbits. There are no adequate and well-controlled studies in pregnant women. Acetazolamide should be used in pregnancy only if the potential benefit justifies the potential risk to the fetus.

Nursing Mothers

Because of the potential for serious adverse reactions in nursing infants from acetazolamide, a decision should be made whether to discontinue nursing or to discontinue the drug taking into account the importance of the drug to the mother. Acetazolamide should only be used by nursing women if the potential benefit justifies the potential risk to the child.

Pediatric Use

The safety and effectiveness of Acetazolamide Extended-Release Capsules in pediatric patients below the age of 12 years have not been established. Growth retardation has been reported in children receiving long-term therapy, believed secondary to chronic acidosis.

Geriatric Use

Metabolic acidosis, which can be severe, may occur in the elderly with reduced renal function. In general, dose selection for an elderly patient should be cautious, usually starting at the low end of the dosing range, reflecting the greater frequency of decreased hepatic, renal, or cardiac function, and concomitant disease or other drug therapy.

ADVERSE REACTIONS

Body as a whole:

Headache, malaise, fatigue, fever, pain at injection site, flushing, growth retardation in children, flaccid paralysis, anaphylaxis.

Digestive:

Gastrointestinal disturbances such as nausea, vomiting, diarrhea.

Hematological/Lymphatic:

Blood dyscrasias such as aplastic anemia, agranulocytosis, leukopenia, thrombocytopenic purpura, melena.

Hepato-biliary disorders:

Abnormal liver function, cholestatic jaundice, hepatic insufficiency, fulminant hepatic necrosis.

Metabolic/Nutritional:

Metabolic acidosis, electrolyte imbalance, including hypokalemia, hyponatremia, osteomalacia with long-term phenytoin therapy, loss of appetite, taste alteration, hyper/hypoglycemia.

Nervous:

Drowsiness, paresthesia (including numbness and tingling of extremities and face), depression, excitement, ataxia, confusion, convulsions, dizziness.

Skin:

Allergic skin reactions including urticaria, photosensitivity, Stevens-Johnson syndrome, toxic epidermal necrolysis.

Otologic:

Hearing disturbances, tinnitus.

Eye Disorders:

Choroidal effusion, choroidal detachment, transient myopia. Transient myopia is the result of forward movement of the ciliary body leading to a narrowing of the angle.

Urogenital:

Crystalluria, increased risk of nephrolithiasis with long-term therapy, hematuria, glycosuria, renal failure, polyuria.

To report SUSPECTED ADVERSE REACTIONS, contact Westminster Pharmaceuticals, LLC at 1-844-221-7294 or FDA at 1-800-FDA-1088 or www.fda.gov/medwatch.

OVERDOSAGE

No specific antidote is known. Treatment should be symptomatic and supportive.

Electrolyte imbalance, development of an acidotic state, and central nervous system effects might be expected to occur. Serum electrolyte levels (particularly potassium) and blood pH levels should be monitored. Supportive measures are required to restore electrolyte and pH balance. The acidotic state can usually be corrected by the administration of bicarbonate.

Despite its high intraerythrocytic distribution and plasma protein binding properties, Acetazolamide may be dialyzable. This may be particularly important in the management of acetazolamide overdosage when complicated by the presence of renal failure.

DOSAGE AND ADMINISTRATION

Glaucoma

The recommended dosage is 1 capsule (500 mg) two times a day. Usually 1 capsule is administered in the morning and 1 capsule in the evening. It may be necessary to adjust the dose, but it has usually been found that dosage in excess of 2 capsules (1 g) does not produce an increased effect. The dosage should be adjusted with careful individual attention both to symptomatology and intraocular tension. In all cases, continuous supervision by a physician is advisable.

In those unusual instances where adequate control is not obtained by the twice-a-day administration of Acetazolamide Extended-Release Capsules, the desired control may be established by means of acetazolamide (tablets or parenteral). Use tablets or parenteral in accordance with the more frequent dosage schedules recommended for these dosage forms, such as 250 mg every four hours, or an initial dose of 500 mg followed by 250 mg or 125 mg every four hours, depending on the case in question.

Acute Mountain Sickness

Dosage is 500 mg to 1000 mg daily, in divided doses using tablets or extended-release capsules as appropriate. In circumstances of rapid ascent, such as in rescue or military operations, the higher dose level of 1000 mg is recommended. It is preferable to initiate dosing 24 to 48 hours before ascent and to continue for 48 hours while at high altitude, or longer as necessary to control symptoms.

HOW SUPPLIED

Acetazolamide Extended-Release Capsules are available as 500 mg:

Size '00' capsules with light green opaque body, imprinted 'HP120' in black ink on light green opaque cap. Contains white to off white pellets.

Available in bottles of 100, NDC 69367-209-01

STORAGE AND HANDLING

Store at 20°C to 25°C (68°F to 77°F) [See USP Controlled Room Temperature].

Manufactured by:
USV Private Limited
Daman – 396210, India

Distributed by:
Westminster Pharmaceuticals, LLC
Nashville, TN 37217

Rev. 3/2025

XXXXXXXX

PRINCIPAL DISPLAY PANEL - 500 mg Capsule Bottle Label

NDC 69367-209-01
Rx only

AcetaZOLAMIDE
Extended-Release
Capsules

500 mg

100 Capsules

Westminster
Pharmaceuticals